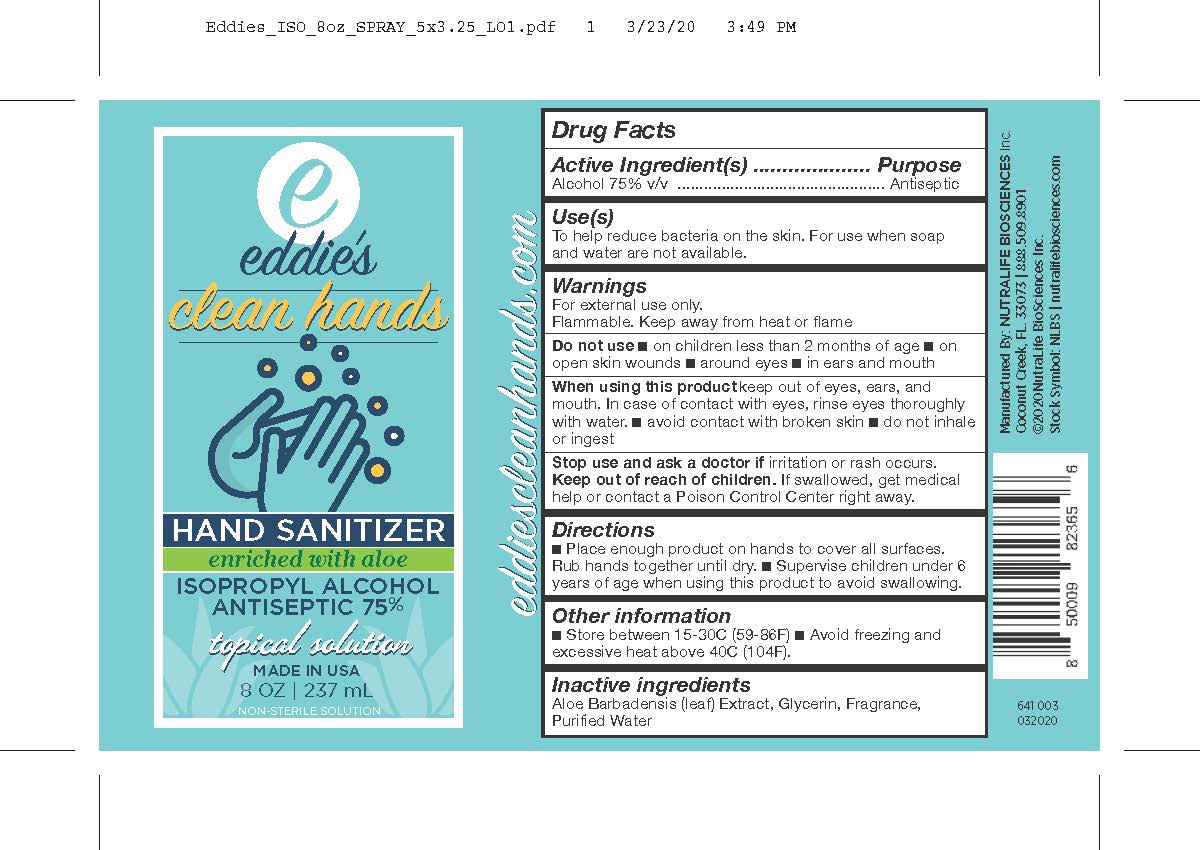 DRUG LABEL: Eddies Hand Sanitizer
NDC: 73761-101 | Form: SPRAY
Manufacturer: Nutralife Biosciences, Inc.
Category: otc | Type: HUMAN OTC DRUG LABEL
Date: 20200421

ACTIVE INGREDIENTS: ISOPROPYL ALCOHOL 177.75 mL/237 mL
INACTIVE INGREDIENTS: ALOE VERA LEAF; GLYCERIN; WATER

Eddie's Spray Hand Sanitizer 8oz Nutralife

Active Ingredient

Alcohol 75%

Purpose

Antiseptic

Uses

To help reduce bacteria on the skin. For use when soap and water are not available.

Warnings

For External Use only

Flammable. Keep away from heat or flame

Do not Use

-On children less than 2 months of age- On open skin wounds -around eyes -in ears and mouth

When using this product

Keep out of eyes, ears, and mouth. In case of contact with eyes, rinse eyes thoroughly with water. -avoid contact with broken skin. - do not inhale or ingest

Stop use and ask a doctor if

Irritation or rash occurs

Keep out of reach of children

If swallowed, get medical help or contact a Poison Control Center right away

Directions

-Place enough product on hands to cover all surfaces. Rub hands together until dry. -Supervise children under 6 years of age when using this product to avoid swallowing.

Other Information

Store between 15-30C (59-86F). -Avoid freezing and excessive above 40C (104F)

Inactive Ingredients

Aloe Barbadensis (leaf) Extract, Glycerin, Fragrance, Purified water